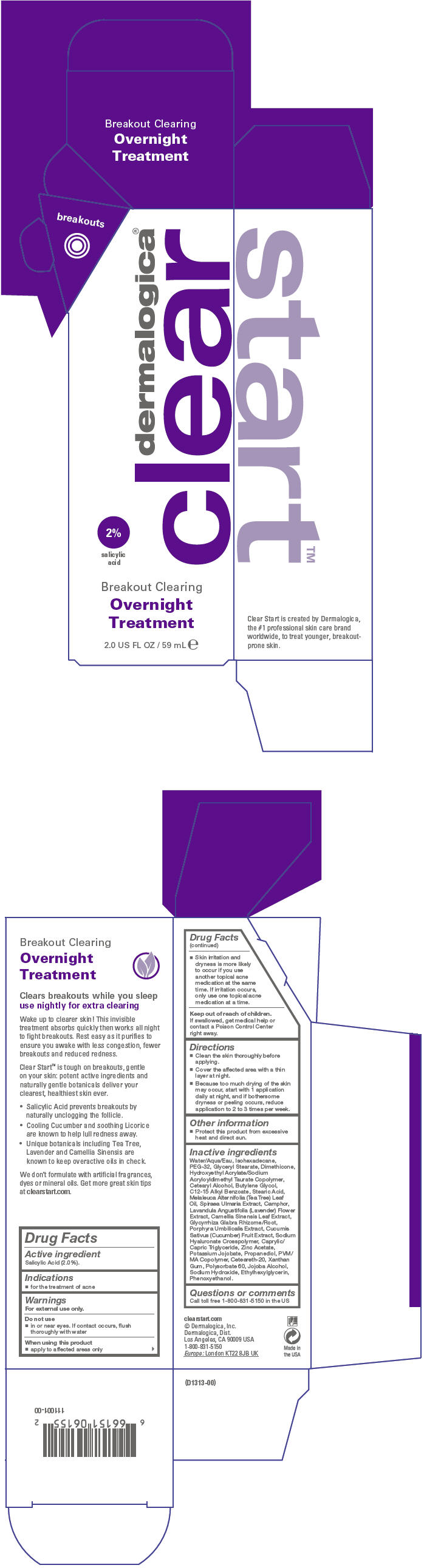 DRUG LABEL: Breakout Clearing Overnight Treatment
NDC: 68479-313 | Form: LOTION
Manufacturer: Dermalogica, Inc.
Category: otc | Type: HUMAN OTC DRUG LABEL
Date: 20140205

ACTIVE INGREDIENTS: Salicylic Acid 20 mg/1 mL
INACTIVE INGREDIENTS: Water; Isohexadecane; POLYETHYLENE GLYCOL 1500; Glyceryl Monostearate; Dimethicone; HYDROXYETHYL ACRYLATE/SODIUM ACRYLOYLDIMETHYL TAURATE COPOLYMER (45000 MPA.S AT 1%); Cetostearyl Alcohol; Butylene Glycol; Alkyl (C12-15) Benzoate; Stearic Acid; Tea Tree Oil; FILIPENDULA ULMARIA ROOT; CAMPHOR (SYNTHETIC); Lavandula Angustifolia Flower; Green Tea Leaf; GLYCYRRHIZA GLABRA; Porphyra Umbilicalis; Cucumber; Medium-Chain Triglycerides; Zinc Acetate; Propanediol; Polyoxyl 20 Cetostearyl Ether; Xanthan Gum; Polysorbate 60; Sodium Hydroxide; Ethylhexylglycerin; Phenoxyethanol

Breakout Clearing Overnight Treatment

Drug Facts

Active ingredient

Salicylic Acid (2.0%).

Indications

PURPOSE

- for the treatment of acne

Warnings

For external use only.

Do not use

- in or near eyes. If contact occurs, flush thoroughly with water

When using this product

- apply to affected areas only
- Skin irritation and dryness is more likely to occur if you use another topical acne medication at the same time. If irritation occurs, only use one topical acne medication at a time.

Keep out of reach of children. If swallowed, get medical help or contact a Poison Control Center right away.

Directions

- Clean the skin thoroughly before applying.
- Cover the affected area with a thin layer at night.
- Because too much drying of the skin may occur, start with 1 application daily at night, and if bothersome dryness or peeling occurs, reduce application to 2 to 3 times per week.

Other information

- Protect this product from excessive heat and direct sun.

Inactive ingredients

Water/Aqua/Eau, Isohexadecane, PEG-32, Glyceryl Stearate, Dimethicone, Hydroxyethyl Acrylate/Sodium Acryloyldimethyl Taurate Copolymer, Cetearyl Alcohol, Butylene Glycol, C12-15 Alkyl Benzoate, Stearic Acid, Melaleuca Alternifolia (Tea Tree) Leaf Oil, Spiraea Ulmaria Extract, Camphor, Lavandula Angustifolia (Lavender) Flower Extract, Camellia Sinensis Leaf Extract, Glycyrrhiza Glabra Rhizome/Root, Porphyra Umbilicalis Extract, Cucumis Sativus (Cucumber) Fruit Extract, Sodium Hyaluronate Crosspolymer, Caprylic/ Capric Triglyceride, Zinc Acetate, Potassium Jojobate, Propanediol, PVM/ MA Copolymer, Ceteareth-20, Xanthan Gum, Polysorbate 60, Jojoba Alcohol, Sodium Hydroxide, Ethylhexylglycerin, Phenoxyethanol.

Questions or comments

Call toll free 1-800-831-5150 in the US

PRINCIPAL DISPLAY PANEL - 59 mL Tube Carton

dermalogica®
clear

2%
salicylic
acid

Breakout Clearing
Overnight
Treatment

2.0 US FL OZ / 59 mL e